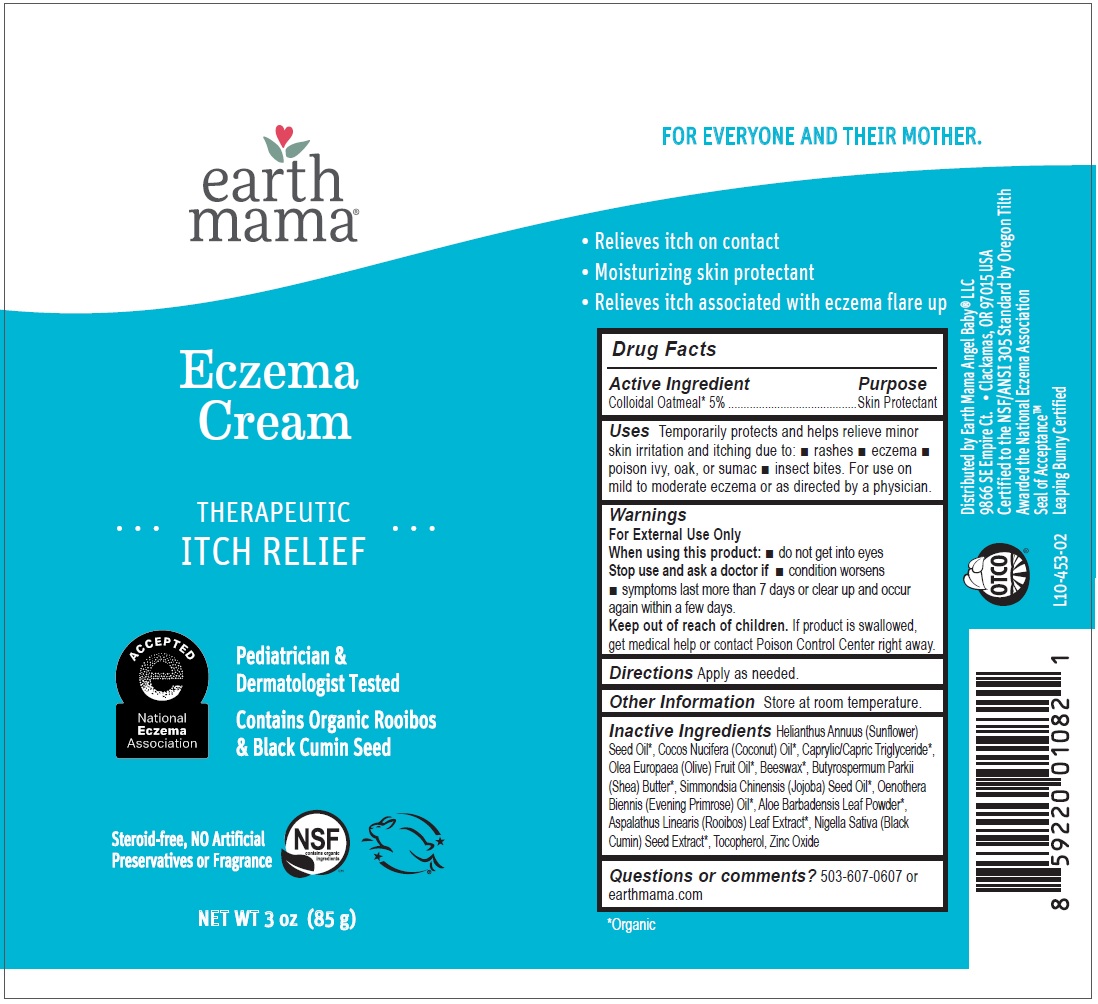 DRUG LABEL: Earth Mama Eczema Cream
NDC: 72812-151 | Form: CREAM
Manufacturer: Earth Mama Angel Baby, LLC
Category: otc | Type: HUMAN OTC DRUG LABEL
Date: 20250812

ACTIVE INGREDIENTS: OATMEAL 50 mg/1 g
INACTIVE INGREDIENTS: SUNFLOWER OIL; COCONUT OIL; MEDIUM-CHAIN TRIGLYCERIDES; OLIVE OIL; YELLOW WAX; SHEA BUTTER; JOJOBA OIL; EVENING PRIMROSE OIL; ALOE VERA LEAF; ASPALATHUS LINEARIS LEAF; NIGELLA SATIVA SEED; TOCOPHEROL; ZINC OXIDE

earth mama®Eczema Cream

Active Ingredient

Colloidal Oatmeal* 5%

Purpose

Skin Protectant

Uses

Temporarily protects and helps relieve minor skin irritation and itching due to: • rashes • eczema • poison ivy, oak, or sumac • insect bites. For use on mild to moderate eczema or as directed by a physician.

Warnings

For External Use Only

When using this product: • do not get into eyes

Stop use and ask a doctor if • condition worsens • symptoms last more than 7 days or clear up and occur again within a few days.

Keep out of reach of children. If product is swallowed, get medical help or contact Poison Control Center right away.

Directions

Apply as needed.

Other Information

Store at room temperature.

Inactive Ingredients

Helianthus Annuus (Sunflower) Seed Oil*, Cocos Nucifera (Coconut) Oil*, Caprylic/Capric Triglyceride*, Olea Europaea (Olive) Fruit Oil*, Beeswax*, Butyrospermum Parkii (Shea) Butter*, Simmondsia Chinensis (Jojoba) Seed Oil*, Oenothera Biennis (Evening Primrose) Oil*, Aloe Barbadensis Leaf Powder*, Aspalathus Linearis (Rooibos) Leaf Extract*, Nigella Sativa (Black Cumin) Seed Extract*, Tocopherol, Zinc Oxide

*Organic

Questions or comments?

503-607-0607 or earthmama.com

THERAPEUTIC

ITCH RELIEF

Pediatrician &Dermatologist Tested

Contains Organic Rooibos& Black Cumin Seed

Steroid-free, NO Artificial Preservatives or Fragrance

NSF
contains organic ingredients

FOR EVERYONE AND THEIR MOTHER.

• Relieves itch on contact
• Moisturizing skin protectant
• Relieves itch associated with eczema flare up

Distributed by Earth Mama Angel Baby®LLC
9866 SE Empire Ct. • Clackamas, OR 97015 USA

Certified to the NSF/ANSI 305 Standard by Oregon Tilth

Awarded the National Eczema Association

Seal of AcceptanceTM

Leaping Bunny Certified